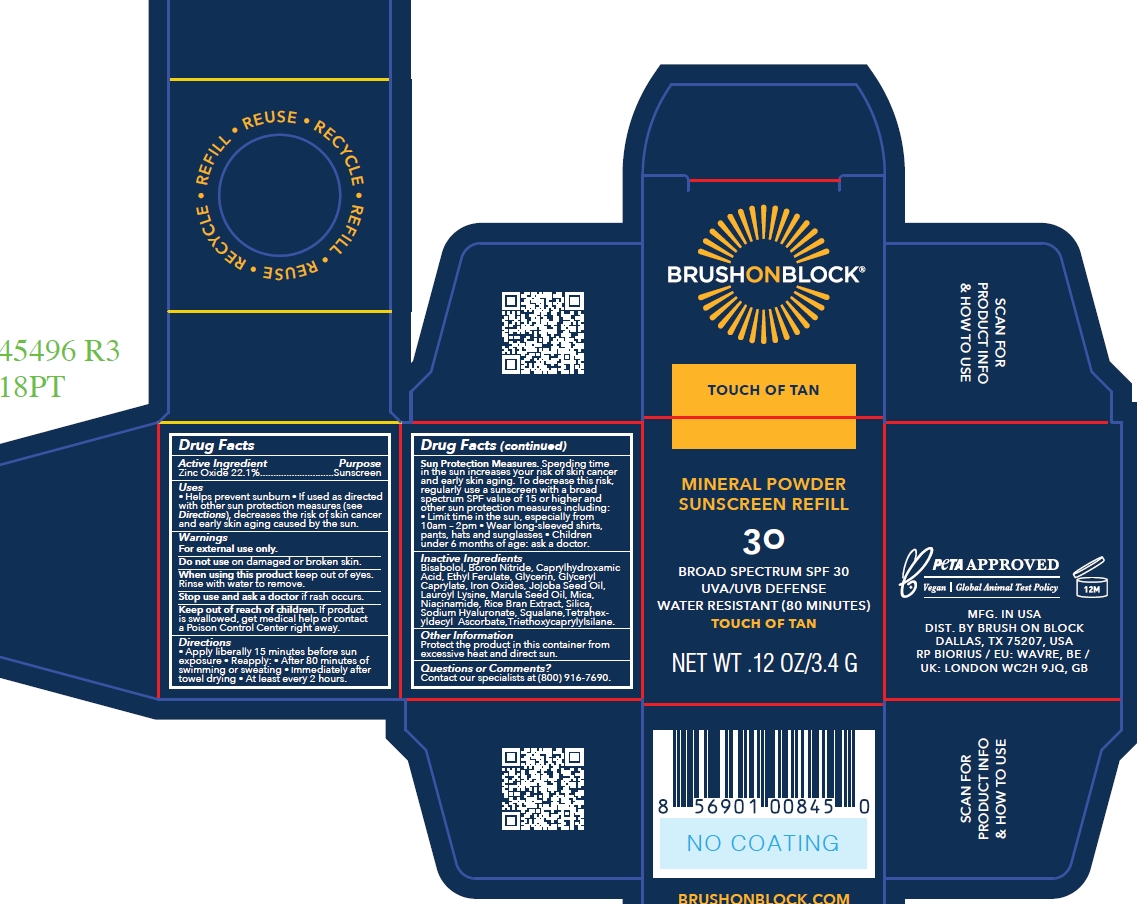 DRUG LABEL: Brush On Block SPF 30 Mineral Powder Touch of Tan Zinc Only - REFILL
NDC: 58274-029 | Form: POWDER
Manufacturer: SPF Ventures, LLC
Category: otc | Type: HUMAN OTC DRUG LABEL
Date: 20250415

ACTIVE INGREDIENTS: ZINC OXIDE 22.1 g/100 g
INACTIVE INGREDIENTS: BORON NITRIDE; TRIETHOXYCAPRYLYLSILANE; SIMMONDSIA CHINENSIS (JOJOBA) SEED OIL; CI 77491; ORYZA SATIVA (RICE) BRAN; MICA; LAUROYL LYSINE; BISABOLOL; SQUALANE; CAPRYLHYDROXAMIC ACID; SODIUM HYALURONATE; ETHYL FERULATE; NIACINAMIDE; GLYCERYL CAPRYLATE; TETRAHEXYLDECYL ASCORBATE; SCLEROCARYA BIRREA SEED OIL; GLYCERIN; CI 77499; SILICA; CI 77492

Brush On Block SPF 30 Mineral Powder Touch of Tan Zinc Only

Active Ingredients

Zinc Oxide 22.1%

Purpose

Sunscreen

Uses

- Helps prevent sunburn
- If used as directed with other sun protection measures (see Directions), decreases the risk of skin cance and early skin aging caused by the sun.

Warnings

For external use only.

Do not use on damaged or broken skin.

When using this product keep out of eyes. Rinse with water to remove.

Stop use and ask a doctor is rash occurs.

Keep out of reach of children

If product is swallowed, get medical help or contact a Poison Control Center right away.

Directions

- Apply liberally 15 minutes before sun expore
- Reapply: After 80 minutes of swimming or sweating; Immediately after towel drying; At least every 2 hours. Sun Protection Measures. Spending time in the sub increase your risk of skin cancer and early skin aging. To decrease this risk, regularly use a sunscreen with s broad spectrum SPF value of 15 or higher and other sun protection measures including:Limit time in the sun, especially from 10am-2pm; Wear long-sleeved shirts, pants, hats and subglasses; Children under 6 months of age: ask a doctor.

Inactive ingredients

Sodium hyaluronate

Niacinimide

Mica

Lauroyl lysine

Boron nitride

Silica

Triethoxycaprylylsilane

Ethyl ferulate

Oryza sativa (rice) bran extract

Iron oxides (CI 77492)

Iron oxides (CI 77499)

Iron oxides (CI 77491)

Bisabolol

Squalane

Simmondsia chinensis (jojoba) seed oil

Tetrahexyldecyl ascorbate

Sclerocarya birrea seed oil

Glyceryl caprylate

Glycerin

Caprylhydroxamic acid